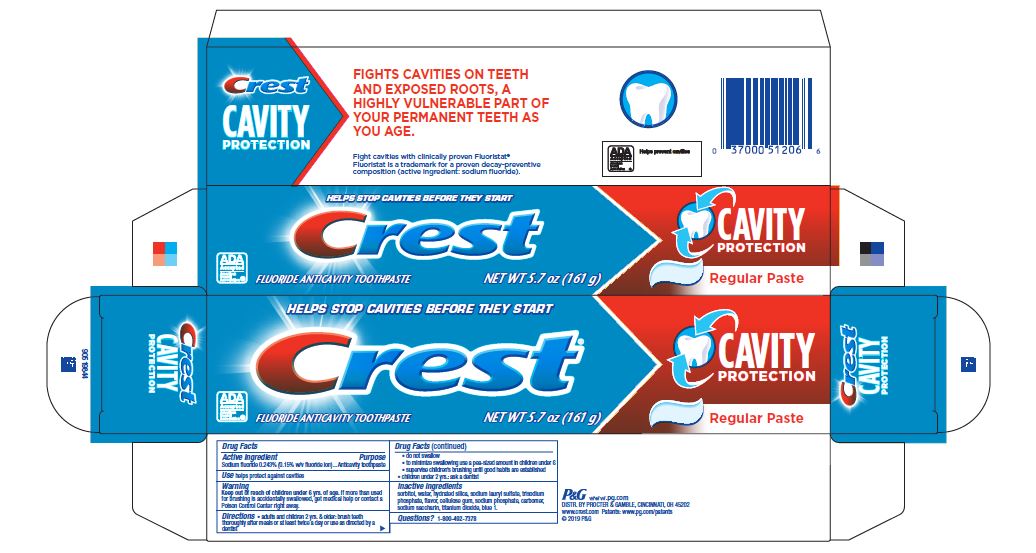 DRUG LABEL: Crest Cavity Protection Regular
NDC: 37000-005 | Form: PASTE, DENTIFRICE
Manufacturer: The Procter & Gamble Manufacturing Company
Category: otc | Type: HUMAN OTC DRUG LABEL
Date: 20251217

ACTIVE INGREDIENTS: SODIUM FLUORIDE 1.5 mg/1 g
INACTIVE INGREDIENTS: CARBOXYPOLYMETHYLENE; SODIUM LAURYL SULFATE; SODIUM PHOSPHATE; TITANIUM DIOXIDE; FD&C BLUE NO. 1; SACCHARIN SODIUM; CARBOXYMETHYLCELLULOSE SODIUM, UNSPECIFIED FORM; SORBITOL; WATER; HYDRATED SILICA; SODIUM PHOSPHATE, TRIBASIC, ANHYDROUS

Crest
Cavity
Protection

Drug Facts

Active ingredient

Sodium fluoride 0.243% (0.15% w/v fluoride ion)

Purpose

Anticavity toothpaste

Use

helps protect teeth and roots against cavities

Warnings

Keep out of reach of children under 6 yrs. of age. If more than used for brushing is accidentally swallowed, get medical help or contact a Poison Control Center right away.

Directions

- adults and children 2 yrs. & older: brush teeth thoroughly after meals or at least twice a day or use as directed by a dentist
  - do not swallow
  - to minimize swallowing use a pea-sized amount in children under 6
  - supervise children's brushing until good habits are established
- children under 2 yrs.: ask a dentist

Inactive ingredients

sorbitol, water, hydrated silica, sodium lauryl sulfate, trisodium phosphate, flavor, cellulose gum, sodium phosphate, carbomer, sodium saccharin, titanium dioxide, blue 1

Questions?

1-800-492-7378

Dist. by Procter & Gamble, Cincinnati OH 45202

www.crest.com

PRINCIPAL DISPLAY PANEL - 161 g Carton

HELPS STOP CAVITIES BFORE THEY START

Crest®

ADA
ACCEPTED
American
Dental
Association®

FLUORIDE ANTICAVITY TOOTHPASTE

NET WT 5.7 OZ (161 g)

CAVITY
PROTECTION

Regular Paste